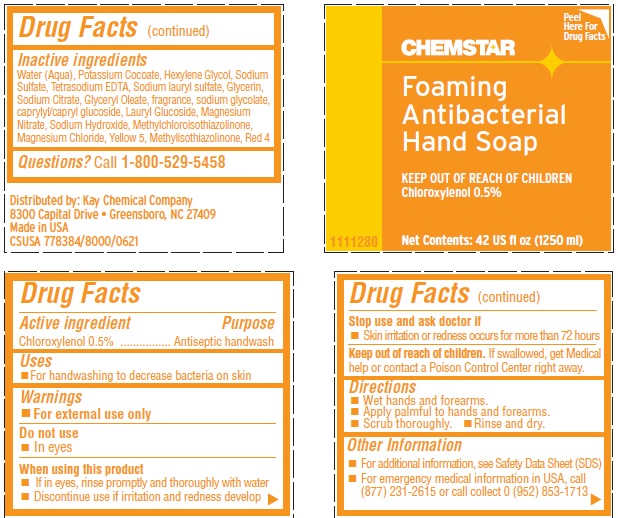 DRUG LABEL: CHEMSTAR
NDC: 47593-688 | Form: SOLUTION
Manufacturer: Ecolab Inc.
Category: otc | Type: HUMAN OTC DRUG LABEL
Date: 20251230

ACTIVE INGREDIENTS: CHLOROXYLENOL 0.5 mg/100 mL
INACTIVE INGREDIENTS: WATER; POTASSIUM COCOATE; HEXYLENE GLYCOL; SODIUM SULFATE; EDETATE SODIUM; SODIUM LAURYL SULFATE; GLYCERIN; ANHYDROUS CITRIC ACID; GLYCERYL OLEATE; SODIUM GLYCOLATE; CAPRYLYL/CAPRYL OLIGOGLUCOSIDE; LAURYL GLUCOSIDE; MAGNESIUM NITRATE; SODIUM HYDROXIDE; METHYLCHLOROISOTHIAZOLINONE; MAGNESIUM CHLORIDE; FD&C YELLOW NO. 5; METHYLISOTHIAZOLINONE; FD&C RED NO. 4

Drug Facts

Active ingredient

Chloroxylenol, 0.5%

Purpose

Antiseptic handwash

Uses

- for handwashing to decrease bacteria on the skin

Warnings

For external use only

Do not use

- in eyes

When using this product

- if in eyes, rinse promptly and thoroughly with water
- discontinue use if irritation and redness develop

Stop use and ask a doctor if

- skin irritation or redness occurs for more than 72 hours

Keep out of reach of children. If swallowed, get medical help or contact a Poison Control Center right away.

Directions

- wet hands and forearms
- dispense a palmful to hands and forearms
- scrub thoroughly
- Rinse and dry

Other information

- for additional information, see Safety Data Sheet (SDS)
- for emergency medical information in USA, call (877) 231-2615 or call collect 0 (952) 853-1713

INACTIVE INGREDIENT

Inactive ingredients Water (Aqua), Potassium Cocoate, Hexylene Glycol, Sodium Sulfate, Tetrasodium EDTA, Sodium lauryl sulfate, Glycerin, Sodium Citrate, Glyceryl Oleate, fragrance, sodium glycolate, caprylyl/capryl glucoside, Lauryl Glucoside, Magnesium Nitrate, Sodium Hydroxide, Methylchloroisothiazolinone, Magnesium Chloride, Yellow 5, Methylisothiazolinone, Red 4

Questions? call 1.800.529-5458

Principal display panel and representative label

CHEMSTAR

Foaming Antibacterial

Hand Soap

KEEP OUT OF REACH OF CHILDREN

Chloroxylenol 0.5%

Net Contents 42 US fl ox (1250 mL)

111280

Distributed by: Kay Chemical Company

8300 Capital Drive - Greensboro, NC 27409

Made in USA

CSUSA 779394/8000/0621